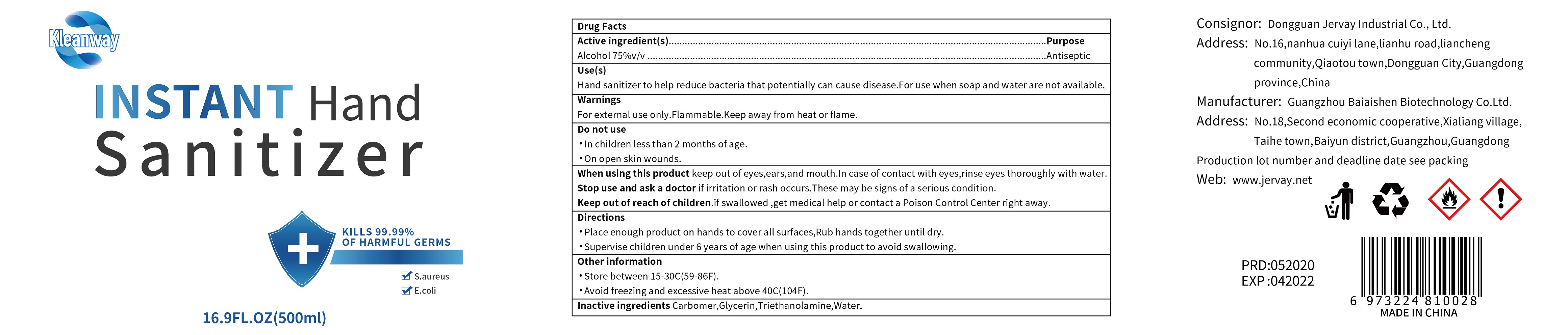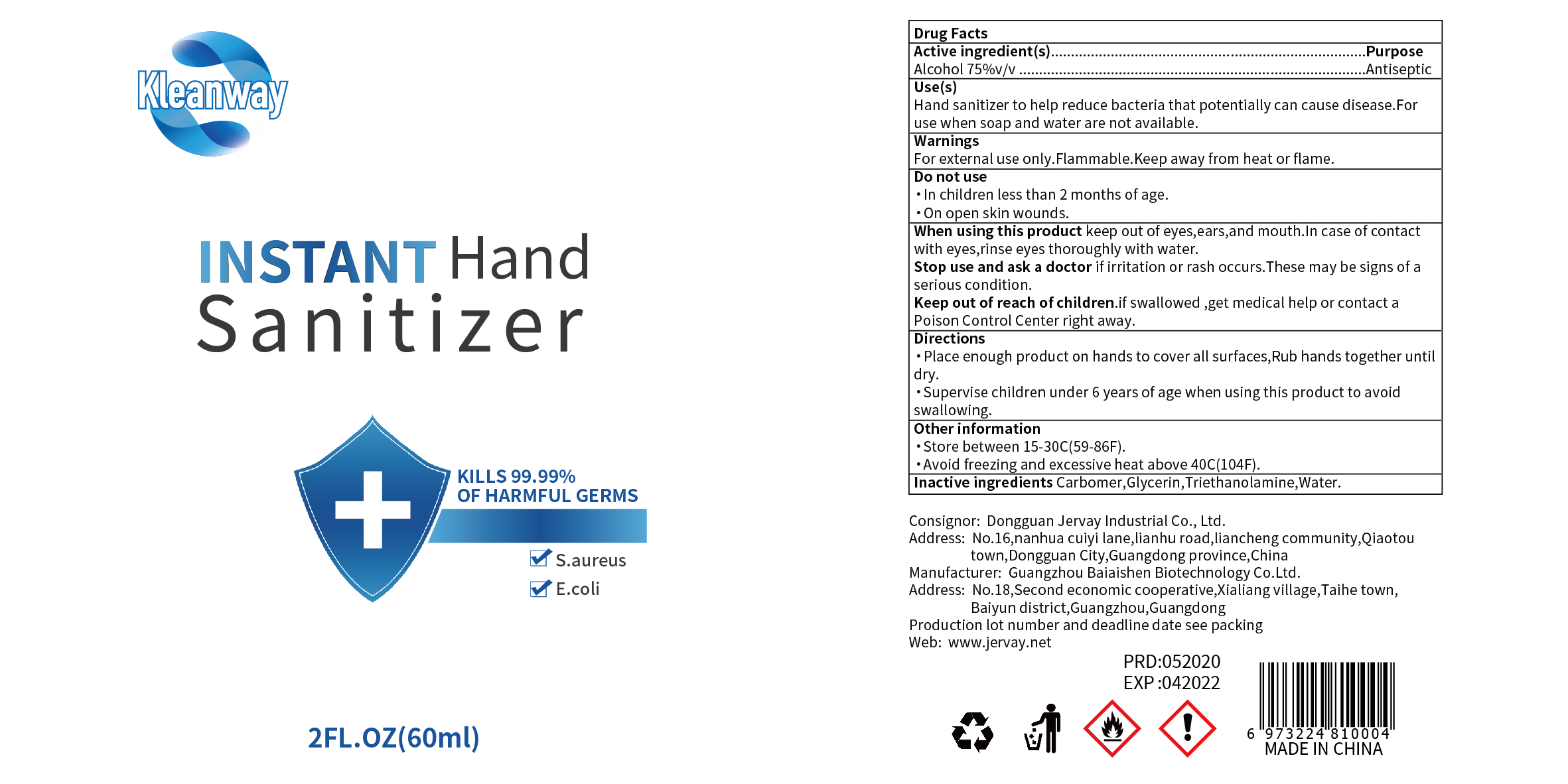 DRUG LABEL: Vivacious Instant Hand Sanitizer
NDC: 77572-001 | Form: GEL
Manufacturer: Global 1 Wholesale Merchant Services, Inc.
Category: otc | Type: HUMAN OTC DRUG LABEL
Date: 20200514

ACTIVE INGREDIENTS: ALCOHOL 75 mL/1 mL
INACTIVE INGREDIENTS: WATER; CARBOMER HOMOPOLYMER, UNSPECIFIED TYPE; GLYCERIN; TROLAMINE

Active Ingredients

Ethanol 75 ± 5% (V/V)

Purpose

Antiseptic

Use

To reduce bacteria on hand

Warnings

For External Use Only

Flammable. Keep away from Heat or Flame

Do Not Use

In children less than 2 months of age

On open skin wounds

WHEN USING

Keep out of eyes, ears, and mouth. In case of contact with eyes, rinse thoroughly with water

Stop use and ask a doctorif irritation or rash occur

Keep out of reach of children. If swallowed, get medical help or contact a Poison Control Center right away

Directions

Place enough amount of product on hands to cover all surface.

Rub hands until dry.

Supervise children under 6 years old when using this product to avoid swallowing.

Other information

Store between 15 - 30°C (59 - 86°F)

Avoid Freezing and Excessive Heat above 40°C (104°F)

Inactive ingredients

Aqua (Water), Carbomer, Glycerol, Triethanolamine

PACKAGE LABEL

60 mL - NDC 77572-001-35

500 mL - NDC 77572-001-40